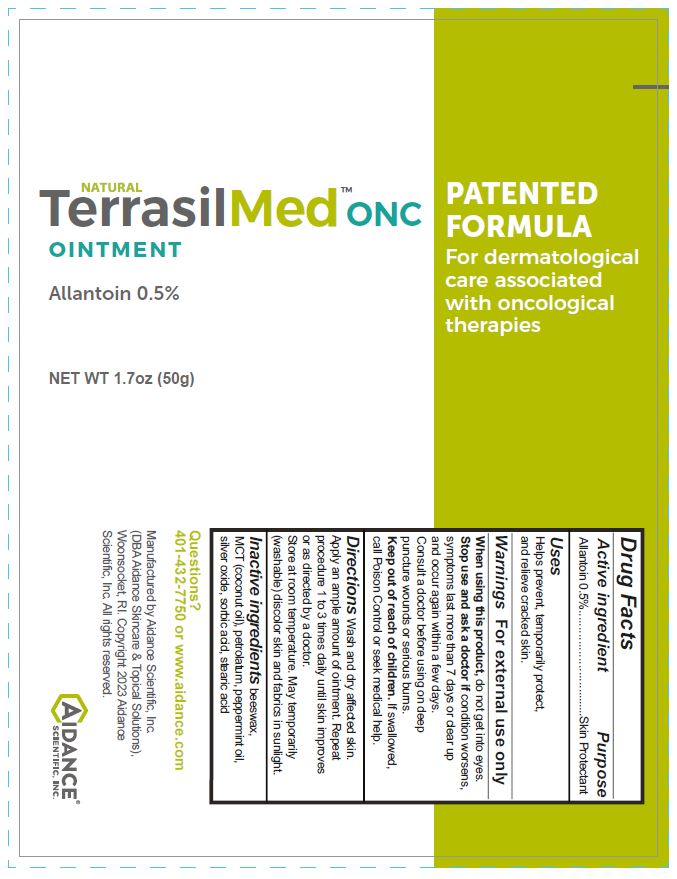 DRUG LABEL: TerrasilMed ONC
NDC: 24909-029 | Form: OINTMENT
Manufacturer: Aidance Scientific, Inc., DBA Aidance Skincare & Topical Solutions
Category: otc | Type: HUMAN OTC DRUG LABEL
Date: 20241125

ACTIVE INGREDIENTS: ALLANTOIN 0.5 g/100 g
INACTIVE INGREDIENTS: YELLOW WAX; COCONUT OIL; PEPPERMINT OIL; PETROLATUM; SILVER OXIDE; SORBIC ACID; STEARIC ACID

24909-029 TerrasilMed ONC

Active ingredient

Allantoin 0.5%

Purpose

Skin Protectant

Uses

Helps prevent, temporarily protect, and relieve cracked skin.

Warnings

For external use only. When using this product, do not get into eyes. Stop use and ask a doctor ifcondition worsens, symptoms last more than 7 days or clear up and occur again within a few days. Consult a doctor before using on deep puncture wounds or serious burns.

Keep out of reach of children.

OTHER SAFETY INFORMATION

If swallowed, call Poison Control or seek medical help.

Directions

Wash and dry affected skin. Apply an ample amount of ointment. Repeat procedure 1 to 3 times daily until skin improves or as directed by a doctor. Store at room temperature. May temporarily (washable) discolor skin and fabrics in sunlight.

Inactive ingredients

beeswax, MCT (coconut oil), peppermint oil, petrolatum, silver oxide, sorbic acid, stearic acid

Other information

Questions? 401-432-7750 or www.aidance.com